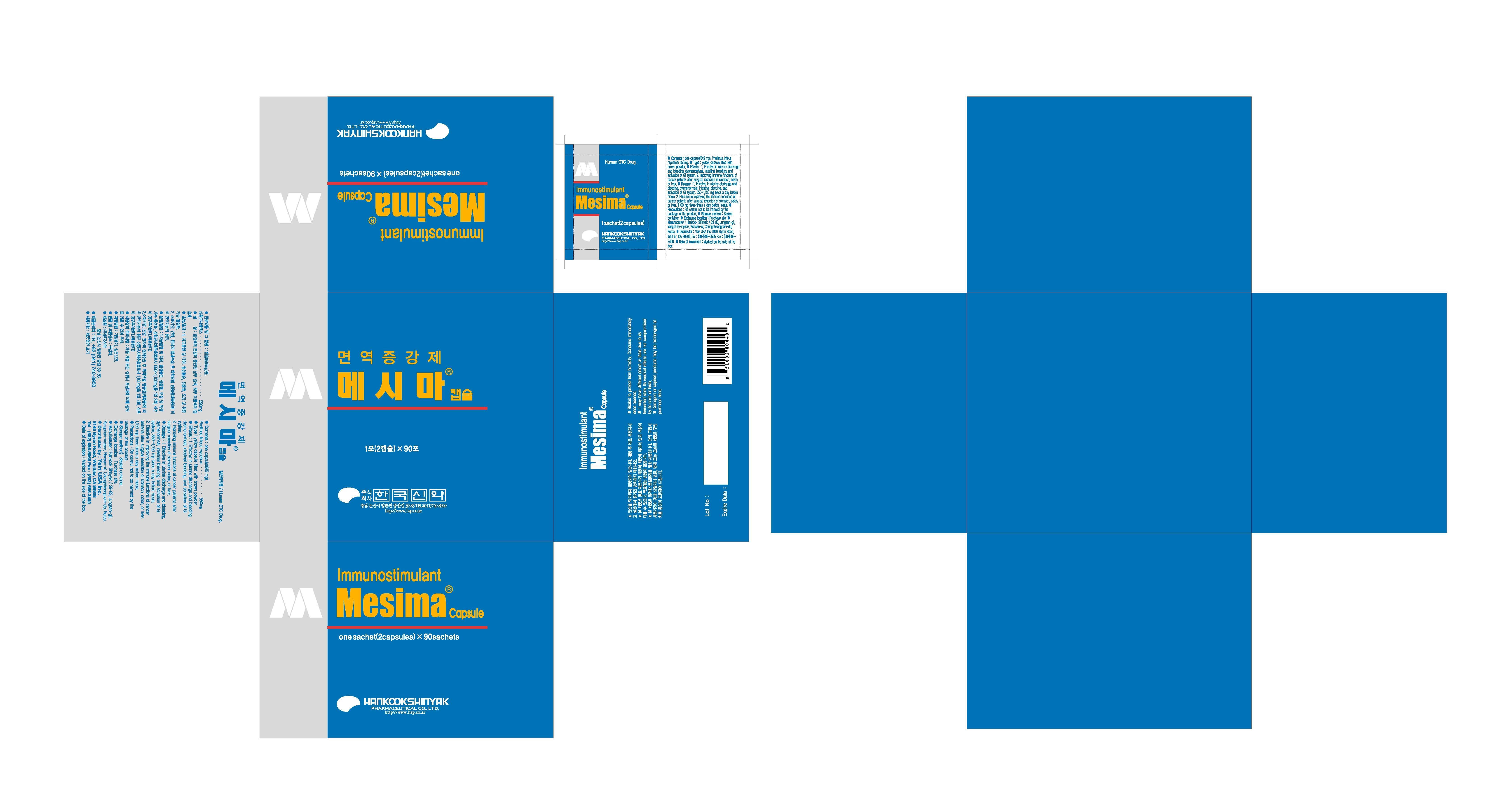 DRUG LABEL: Mesima
                
NDC: 53144-1001 | Form: CAPSULE
Manufacturer: Yein Trading & Global Co., Ltd
Category: otc | Type: HUMAN OTC DRUG LABEL
Date: 20130227

ACTIVE INGREDIENTS: PHELLINUS LINTEUS MYCELIUM 1.1 1/1 1
INACTIVE INGREDIENTS: LACTOSE; ICODEXTRIN

Drug Facts

ACTIVE INGREDIENT

phellinus linteus mycelium

INACTIVE INGREDIENT

lactose, dextrin

PURPOSE

- effective in uterine discharge and bleeding, dysmenorrheal, intestinal bleeding and activation of GI system
-improving the immune functions of cancer patients after surgical resection of stomach, colon, or liver

keep out of reach of the children

INDICATIONS AND USAGE

- effective in uterine discharge and bleeding, dysmenorrheal, intestinal bleeding, and activation of GI system, 550-1100mg twice a day before meals
- effective in improving the immune functions of cancer patients after surgical resection of stomach, colon, or liver, 1100mg three times a day before meals

WARNINGS

- GI system: may cause nausea, vomiting, diarrhea, or abdominal discomfort
- dizziness (one case), headache (one case), and constipation (three cases) were reported during clinical trials

DOSAGE AND ADMINISTRATION

for oral use only